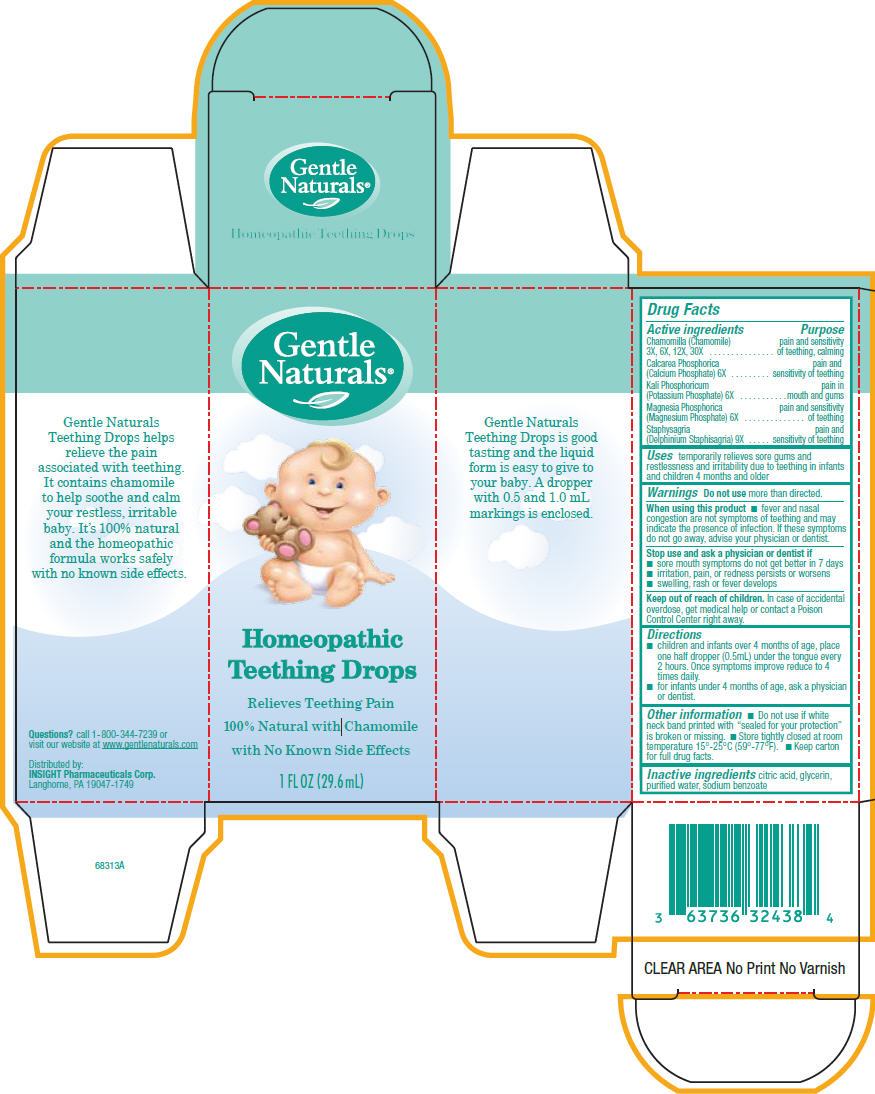 DRUG LABEL: Gentle Naturals
NDC: 63736-318 | Form: LIQUID
Manufacturer: Insight Pharmaceuticals
Category: homeopathic | Type: HUMAN OTC DRUG LABEL
Date: 20100706

ACTIVE INGREDIENTS: Matricaria Recutita 30 [hp_X]/1 mL; Tribasic Calcium Phosphate 6 [hp_X]/1 mL; Potassium Phosphate, Dibasic 6 [hp_X]/1 mL; Magnesium Phosphate, Dibasic Trihydrate 6 [hp_X]/1 mL; Delphinium Staphisagria Seed 9 [hp_X]/1 mL
INACTIVE INGREDIENTS: Citric Acid Monohydrate; Glycerin; Water; Sodium Benzoate

Gentle
Naturals®
Homeopathic
Teething Drops

Drug Facts

ACTIVE INGREDIENT

Active ingredients | Purpose
Chamomilla (Chamomile) 3X, 6X, 12X, 30X | pain and sensitivity of teething, calming
Calcarea Phosphorica (Calcium Phosphate) 6X | pain and sensitivity of teething
Kali Phosphoricum (Potassium Phosphate) 6X | pain in mouth and gums
Magnesia Phosphorica (Magnesium Phosphate) 6X | pain and sensitivity of teething
Staphysagria (Delphinium Staphisagria) 9X | pain and sensitivity of teething

Uses

temporarily relieves sore gums and restlessness and irritability due to teething in infants and children 4 months and older

Warnings

Do not use more than directed.

When using this product

- fever and nasal congestion are not symptoms of teething and may indicate the presence of infection. If these symptoms do not go away, advise your physician or dentist.

Stop use and ask a physician or dentist if

- sore mouth symptoms do not get better in 7 days
- irritation, pain, or redness persists or worsens
- swelling, rash or fever develops

Keep out of reach of children. In case of accidental overdose, get medical help or contact a Poison Control Center right away.

Directions

- children and infants over 4 months of age, place one half dropper (0.5mL) under the tongue every 2 hours. Once symptoms improve reduce to 4 times daily.
- for infants under 4 months of age, ask a physician or dentist.

Other information

- Do not use if white neck band printed with "sealed for your protection" is broken or missing.
- Store tightly closed at room temperature 15°-25°C (59°-77°F).
- Keep carton for full drug facts.

Inactive ingredients

citric acid, glycerin, purified water, sodium benzoate

Questions?

call 1-800-344-7239 or visit our website at www.gentlenaturals.com

Distributed by:

INSIGHT Pharmaceuticals Corp. Langhorne, PA 19047-1749

PRINCIPAL DISPLAY PANEL - 29.6 mL Bottle Carton

Gentle
Naturals®

Homeopathic
Teething Drops

Relieves Teething Pain
100% Natural with Chamomile
with No Known Side Effects

1 FL OZ (29.6 mL)